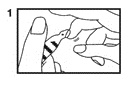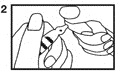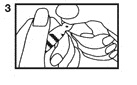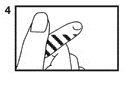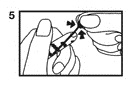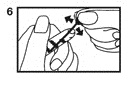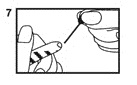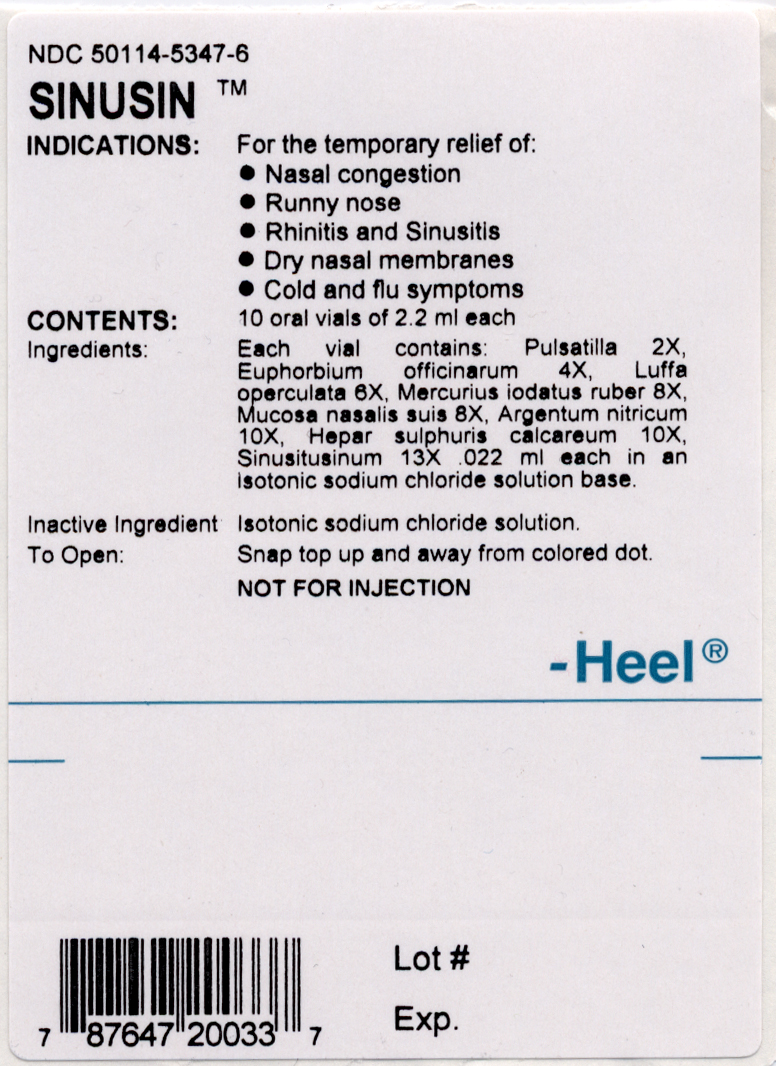 DRUG LABEL: Sinusin
NDC: 51885-3150 | Form: SOLUTION
Manufacturer: Biologische Heilmittel Heel
Category: homeopathic | Type: HUMAN OTC DRUG LABEL
Date: 20100806

ACTIVE INGREDIENTS: PULSATILLA VULGARIS 2 [hp_X]/2.2 mL; EUPHORBIA RESINIFERA RESIN 4 [hp_X]/2.2 mL; LUFFA OPERCULATA FRUIT 6 [hp_X]/2.2 mL; MERCURIC IODIDE 8 [hp_X]/2.2 mL; SUS SCROFA NASAL MUCOSA 8 [hp_X]/2.2 mL; SILVER NITRATE 10 [hp_X]/2.2 mL; CALCIUM SULFIDE 10 [hp_X]/2.2 mL; SINUSITISINUM 13 [hp_X]/2.2 mL

DOSAGE FORM

Oral liquid in vials.

CONTRAINDICATIONS

This drug is contriandicated in patients with a known hypersensitivity to any of its ingredients.

PRECAUTIONS

Pregnancy and nursing mothers: Pregnancy Category C. In general, homeopathic drugs are not known to cause direct or indirect harm to the fetus. However, animal reproduction studies have not been performed and there are no well-controlled studies in pregnant women. In cases of pregnancy or suspected pregnancy, a physician should be consulted before administering this drug. It is not known whether any of the ingredients are excreted in human milk. However because many drugs are excreted in human milk, homeopathic drugs should be administered with caution to nursing mothers.

Pediatric use: Homeopathic drugs can be safely administered to children. See Dosage and Administration.

ADVERSE REACTIONS

In rare cases, patients with a hypersensitivity to any of the ingredients may experience an allergic reaction after oral administration.

DRUG ABUSE AND DEPENDENCE

Not applicable for homeopathic drugs.

OVERDOSAGE

Due to the low concentration of active ingredients, adverse reactions following overdosage are extremely rare. Care must be taken not to exceed the recommended dosage.

WARNINGS

If symptoms persist for more than a few days, a physician should be consulted.

Keep this and all medicines out of the reach of children.

HOW SUPPLIED

Heel vials are supplied in sizes of 1.1ml, 2.0ml and 2.2ml. See carton label for content information.

STORAGE CONDITION

Avoid freezing and excessive heat. Store at room temperature. Protect from direct light.

DOSAGE AND ADMINISTRATION

Adults and children above 6 years: In general 1 vial 1-3 times daily

Children to 6 years: 1/2 the adult dosage

Administration: NOT FOR INJECTION - FOR ORAL ADMINISTRATION ONLY.

Instructions for Opening Vial

1. Vials are pre-scored for easy opening and are marled with a color dot above the neck of the vial. The use of a file is not required. First, ensure that all contents of the vial are below the narrow neck by gently flicking or tapping top of the vial with fingers as in Step (1).

2. Hold vial firmly with one hand with dot toward you (2).

3. With the other hand, snap the vial top slightly upward and away from dot (3). Discard the vial top and be careful of sharp glass edges.

4. To withdraw solution: Tilt open vial until it is nearly horizontal (The vial should be tilted as far as possible without spilling the contents.) (4).

5. Squeeze bulb of the pipette and insert pipette tip into the solution (5).

6. Slowly release pressure on the bulb of the pipette until solution is withdrawn from vial (6).

7. Remove pipette when the solution has been withdrawn (7).

Administer according to carton insert. Discard unused portion.

BE CAREFUL OF SHARP EDGES AFTER OPENING VIAL.

Sinusin OV label.jpg